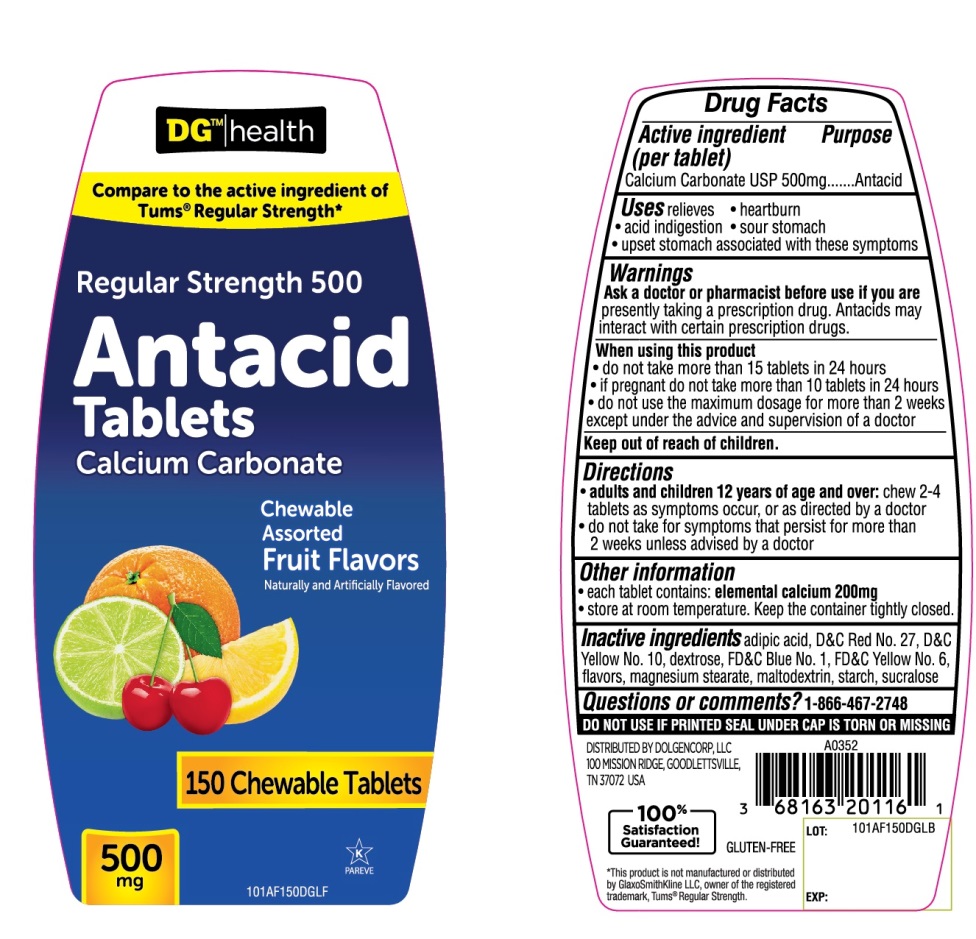 DRUG LABEL: DG Health Regular Strength

NDC: 55910-510 | Form: TABLET, CHEWABLE
Manufacturer: DOLGENCORP, LLC
Category: otc | Type: HUMAN OTC DRUG LABEL
Date: 20250819

ACTIVE INGREDIENTS: CALCIUM CARBONATE 500 mg/1 1
INACTIVE INGREDIENTS: ADIPIC ACID; D&C RED NO. 27; D&C YELLOW NO. 10; DEXTROSE, UNSPECIFIED FORM; FD&C BLUE NO. 1; FD&C YELLOW NO. 6; MAGNESIUM STEARATE; MALTODEXTRIN; STARCH, CORN; SUCRALOSE

Regular Strength Assorted Fruit Antacid Tablets

Active ingredient (per tablet)

Calcium Carbonate USP 500mg

Purpose

Antacid

Uses

relieves

- heartburn
- acid indigestion
- sour stomach
- upset stomach associated with these symptoms

Warnings

Ask a doctor or pharmacist before use if you arepresently taking a prescription drug. Antacids may interact with certain prescription drugs.

When using this product

- do not take more than 15 tablets in 24 hours
- if pregnant do not take more than10 tablets in 24 hours
- do not use the maximum dosage for more than 2 weeks except under the advice and supervision of a doctor.

Directions

- adults and children 12 years of age and over: chew 2-4 tablets as symptoms occur, or as directed by a doctor.
- do not take for symptoms that persist for more than 2 weeks unless advised by a doctor.

Other information

- each tablet contains: elemental calcium 200 mg
- store at room temperature. Keep the container tightly closed.

Inactive ingredients

adipic acid, D&C Red No. 27, D&C Yellow No. 10, dextrose, FD&C Blue No. 1, FD&C Yellow No. 6, flavors, magnesium stearate, maltodextrin, starch, sucralose.

Questions or comments?

1-866-467-2748

SAFETY SEALED: DO NOT USE IF PRINTED SEAL UNDER CAP IS TORN OR MISSING.

Package/Label Principal Display Panel

NDC 55910-510-50

DG™ health

Compare to the active ingredient in Tums®Regular Strength*

Regular Strength 500

Antacid Tablets

Calcium Carbonate

Chewable Assorted Fruit Flavors

Naturally and Artificially Flavored

150 Chewable Tablets

500 mg

GLUTEN-FREE

100% Satisfaction Guaranteed

K PAREVE

DISTRIBUTED BY DOLGENCORP, LLC

100 MISSION RIDGE, GOODLETTSVILLE,

TN 37072 USA

*This product is not manufactured or distributed by GlaxoSmithKline LLC, owner of the registered trademark Tums®Regular Strength.